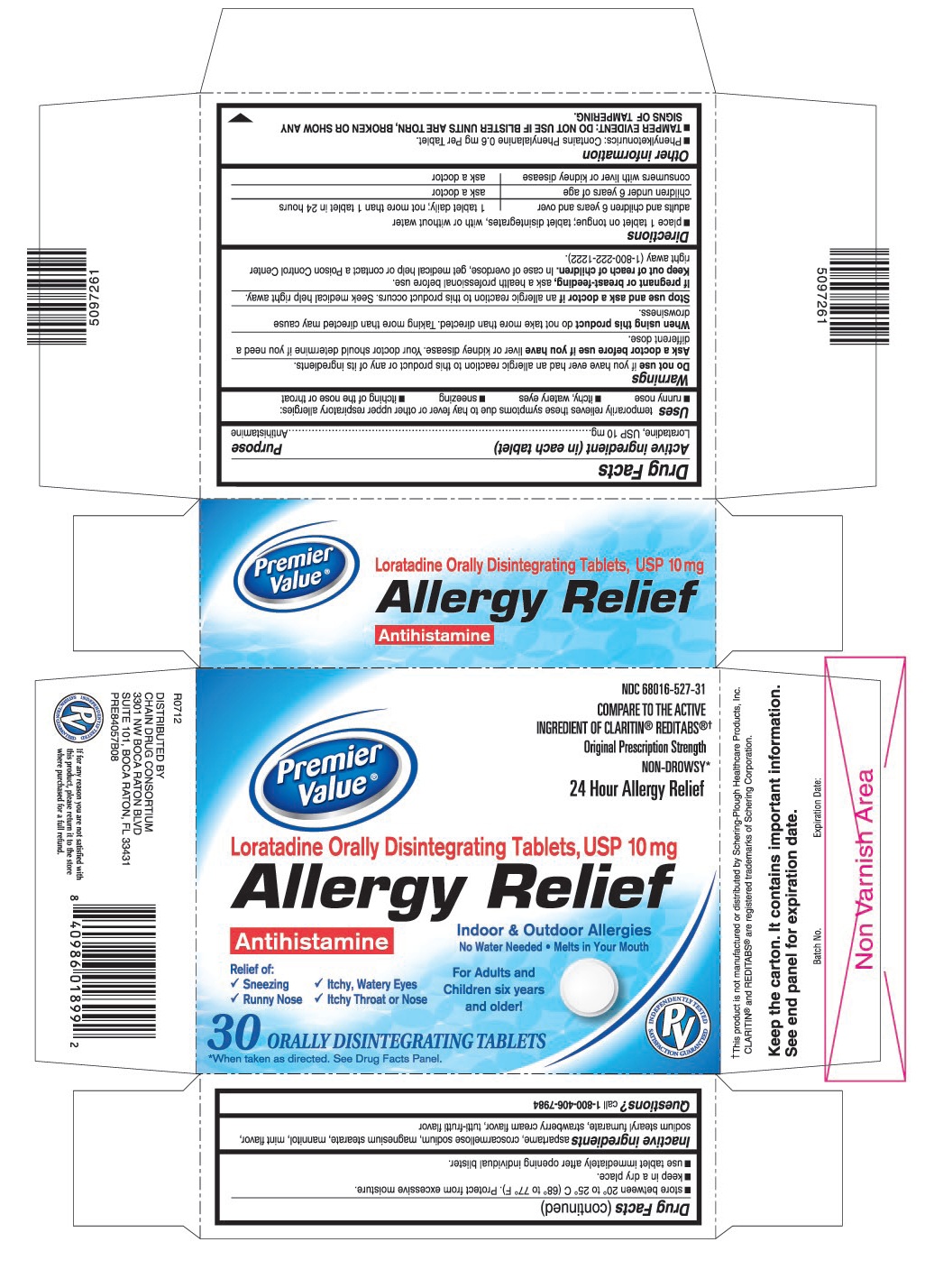 DRUG LABEL: Loratadine ODT
NDC: 68016-527 | Form: TABLET, ORALLY DISINTEGRATING
Manufacturer: Chain Drug Consortium, LLC
Category: otc | Type: HUMAN OTC DRUG LABEL
Date: 20151008

ACTIVE INGREDIENTS: LORATADINE 10 mg/1 1
INACTIVE INGREDIENTS: ASPARTAME; CROSCARMELLOSE SODIUM; MAGNESIUM STEARATE; MANNITOL; SODIUM STEARYL FUMARATE

Drug Facts

ACTIVE INGREDIENT (IN EACH TABLET)

Loratadine, USP 10 mg

PURPOSE

Antihistamine

USES

temporarily relieves these symptoms due to hay fever or other upper respiratory allergies:

- runny nose
- itchy, watery eyes
- sneezing
- itching of the nose or throat

WARNINGS

Do not use

if you have ever had an allergic reaction to this product or any of its ingredients.

Ask a doctor before use if you have

liver or kidney disease. Your doctor should determine if you need a different dose.

When using this product

do not take more than directed. Taking more than directed may cause drowsiness.

Stop use and ask a doctor if

an allergic reaction to this product occurs. Seek medical help right away.

If pregnant or breast-feeding,

ask a health professional before use.

Keep out of reach of children.

In case of overdose, get medical help or contact a Poison Control Center right away (1-800-222-1222).

DIRECTIONS

- place 1 tablet on tongue; tablet disintegrates, with or without water

adults and children 6 years and over | 1 tablet daily; not more than 1 tablet in 24 hours
children under 6 years of age | ask a doctor
consumers with liver or kidney disease | ask a doctor

OTHER INFORMATION

- Phenylketonurics: Contains Phenylalanine 0.6 mg Per Tablet.
- TAMPER EVIDENT: DO NOT USE IF BLISTER UNITS ARE TORN, BROKEN OR SHOW ANY SIGNS OF TAMPERING.
- store between 20° to 25° C (68° to 77° F). Protect from excessive moisture.
- keep in a dry place.
- use tablet immediately after opening individual blister.

INACTIVE INGREDIENTS

aspartame, croscarmellose sodium, fruit flavors, magnesium stearate, mannitol, sodium stearyl fumarate

QUESTIONS?

call 1-800-406-7984

Keep the carton. It contains important information.

See end panel for expiration date.

DISTRIBUTED BY

CHAIN DRUG CONSORTIUM

3301 NW BOCA RATON BLVD

SUITE 101, BOCA RATON, FL 33431

PRINCIPAL DISPLAY PANEL

Premier Value®

NDC 68016-527-31

Original Prescription Strength

NON-DROWSY*

24 Hour Allergy Relief

Loratadine Orally Disintegrating Tablets, 10 mg

Allergy Relief

Antihistamine

Indoor & Outdoor Allergies

No water needed. Melts in your mouth.

Relief of:

- Sneezing
- Itchy, Watery Eyes
- Runny Nose
- Itchy Throat or Nose

For Adults and Children six years and older!

30 ORALLY DISINTEGRATING TABLETS

COMPARE TO THE ACTIVE INGREDIENT OF CLARITIN® REDITABS®†

* When taken as directed. See Drug Facts Panel.

† This product is not manufactured or distributed by Schering-Plough HealthCare Products, Inc. CLARITIN® and REDITABS® are registered trademarks of Schering Corporation.